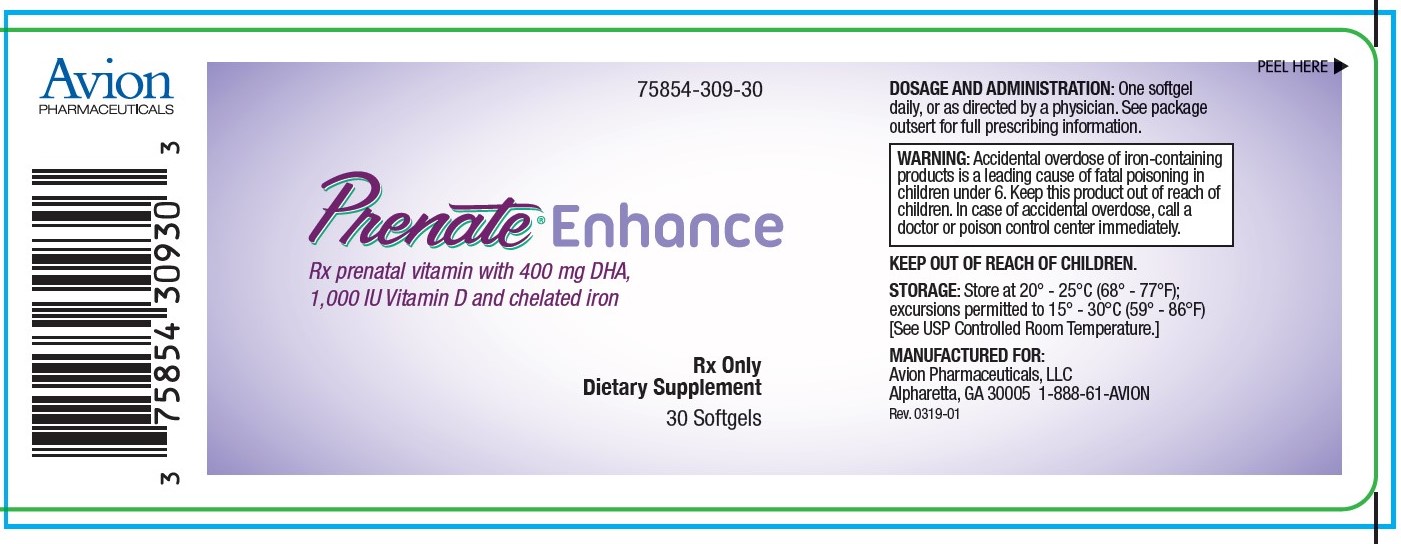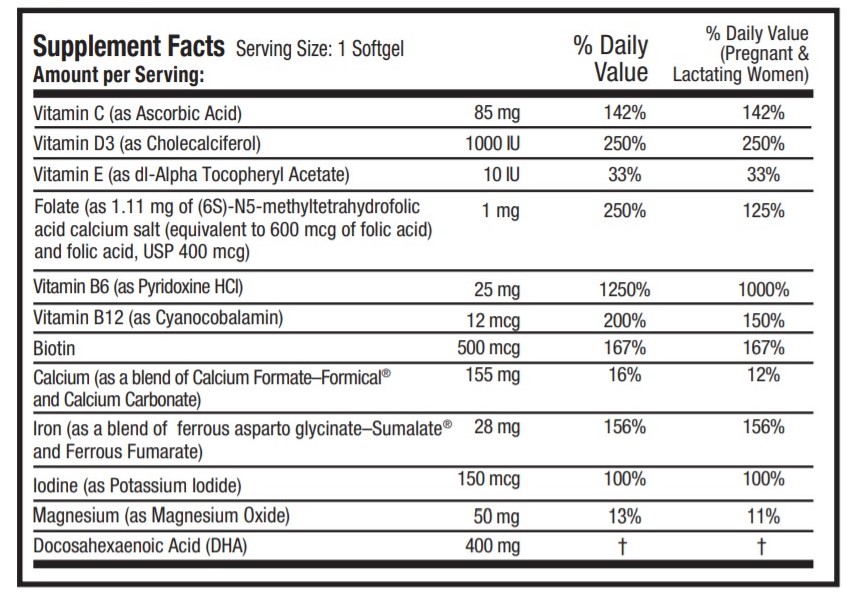 DRUG LABEL: PRENATE Enhance
NDC: 75854-309 | Form: CAPSULE, GELATIN COATED
Manufacturer: Avion Pharmaceuticals, LLC
Category: prescription | Type: HUMAN PRESCRIPTION DRUG LABEL
Date: 20240122

ACTIVE INGREDIENTS: ASCORBIC ACID 85 mg/1 1; CHOLECALCIFEROL 1000 [iU]/1 1; .ALPHA.-TOCOPHEROL ACETATE, DL- 10 [iU]/1 1; FOLIC ACID 1 mg/1 1; PYRIDOXINE HYDROCHLORIDE 25 mg/1 1; CYANOCOBALAMIN 12 ug/1 1; BIOTIN 500 ug/1 1; CALCIUM CARBONATE 155 mg/1 1; FERROUS FUMARATE 28 mg/1 1; POTASSIUM IODIDE 150 mg/1 1; MAGNESIUM OXIDE 50 mg/1 1; DOCONEXENT 400 mg/1 1
INACTIVE INGREDIENTS: GELATIN; GLYCERIN; LECITHIN, SOYBEAN; WHITE WAX; CORN OIL; WATER; FD&C RED NO. 40; TITANIUM DIOXIDE; FD&C BLUE NO. 1

PRENATE® Enhance

Rx postnatal vitamin with 400 mg DHA, 1,000 IU Vitamin D and chelated iron

Rx Only Dietary Supplement

DESCRIPTION

DESCRIPTION: PRENATE® Enhance is a prescription prenatal vitamin that contains 400 mg of DHA and advanced calcium. Each dark purple softgel is imprinted with N on one side and blank on the other.

INACTIVE INGREDIENT

OTHER INGREDIENTS: Gelatin capsule (FD&C Blue # 1, FD&C Red # 40, gelatin, glycerin, purified water, sorbitol, and titanium dioxide), palm shortening, soy lecithin and white beeswax.

INDICATIONS AND USAGE

INDICATIONS: PRENATE® Enhance is a multivitamin/multimineral fatty acid dietary supplement indicated for use in improving the nutritional status of women throughout pregnancy and in the postnatal period for both lactating and nonlactating mothers. PRENATE® Enhance can also be beneficial in improving the nutritional status of women prior to conception.

CONTRAINDICATIONS

CONTRAINDICATIONS: PRENATE® Enhance is contraindicated in patients with a known hypersensitivity to any of the ingredients.

BOXED WARNING

WARNING: Ingestion of more than 3 grams of omega-3 fatty acids (such as DHA) per day has been shown to have potential antithrombotic effects, including an increased bleeding time and International Normalized Ratio (INR). Administration of omega-3 fatty acids should be avoided in patients taking anticoagulants and in those known to have an inherited or acquired predisposition to bleeding.

PRECAUTIONS

PRECAUTIONS: Folic acid alone is improper therapy in the treatment of pernicious anemia and other megaloblastic anemias where Vitamin B12 is deficient. Folic acid in doses above 1.0 mg daily may obscure pernicious anemia in that hematologic remission can occur while neurological manifestations progress.

BOXED WARNING

WARNING: Accidental overdose of iron-containing products is a leading cause of fatal poisoning in children under 6. Keep this product out of reach of children. In case of accidental overdose, call a doctor or poison control center immediately.

ADVERSE REACTIONS

ADVERSE REACTIONS: Allergic sensitization has been reported following both oral and parenteral administration of folic acid.

DOSAGE AND ADMINISTRATION: One softgel daily, or as directed by a physician.

HOW SUPPLIED

HOW SUPPLIED: Bottles of 30 softgels (75854-309-30). The listed product number is not a National Drug Code. Instead, Avion Pharmaceuticals has assigned a product code formatted according to standard industry practice to meet the formatting requirements of pharmacy and healthcare insurance computer systems.

STORAGE AND HANDLING

STORAGE: Store at 20° - 25°C (68° - 77°F); excursions permitted to 15° - 30°C (59° - 86°F) [See USP Controlled Room Temperature.]

WARNINGS

KEEP THIS AND ALL MEDICATIONS OUT OF THE REACH OF CHILDREN.

MANUFACTURED FOR:
Avion Pharmaceuticals, LLC
Atlanta, GA 30005
1-888-61-AVION

Rev. 0319-01

Formical® is a registered trademark of Nephro-Tech 1, LLC, covered by one or more claims of U.S. Patent No. 6,528,542.

Sumalate® is a registered trademark of Albion Laboratories, Inc., covered by one or more claims of U.S. Patent Nos. 5,516,925, 6,716,814, 8,007,846 and 8,425,956.

THESE STATEMENTS HAVE NOT BEEN EVALUATED BY THE FOOD AND DRUG ADMINISTRATION. THIS PRODUCT IS NOT INTENDED TO DIAGNOSE, TREAT, CURE OR PREVENT ANY DISEASE

PRINCIPAL DISPLAY PANEL - 30 Softgel label

75854-309-30

PRENATE®Enhance
Rx postnatal vitamin with probiotics and DHA,

1,000 IU Vitamin D and chelated iron

Rx Only
Dietary Supplement
30 Softgels